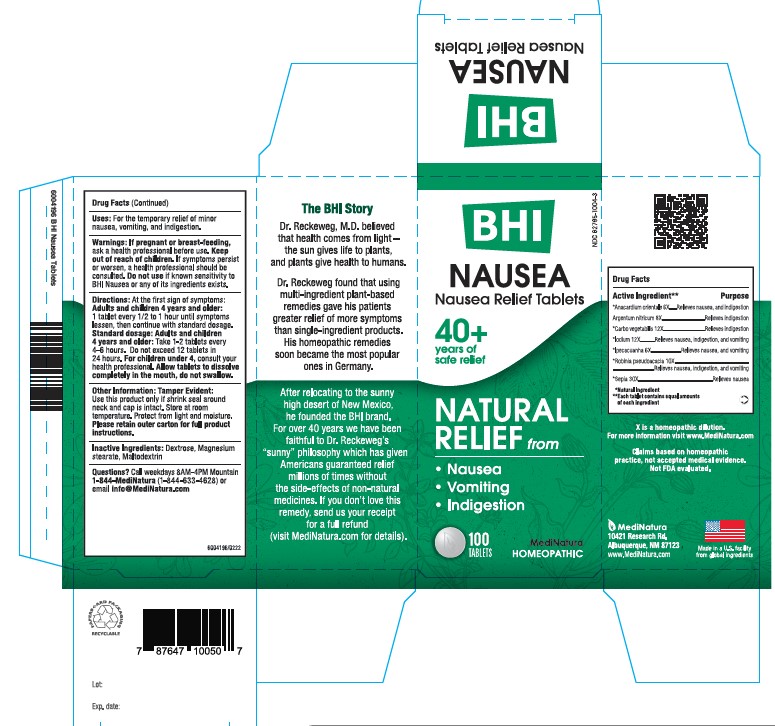 DRUG LABEL: BHI Nausea
NDC: 62795-1004 | Form: TABLET
Manufacturer: MediNatura Inc
Category: homeopathic | Type: HUMAN OTC DRUG LABEL
Date: 20221214

ACTIVE INGREDIENTS: SEMECARPUS ANACARDIUM JUICE 6 [hp_X]/1 1; SILVER NITRATE 8 [hp_X]/1 1; ACTIVATED CHARCOAL 12 [hp_X]/1 1; IPECAC 6 [hp_X]/1 1; IODINE 12 [hp_X]/1 1; ROBINIA PSEUDOACACIA BARK 10 [hp_X]/1 1; SEPIA OFFICINALIS JUICE 30 [hp_X]/1 1
INACTIVE INGREDIENTS: MAGNESIUM STEARATE; MALTODEXTRIN; DEXTROSE

BHI Nausea Tablet

INACTIVE INGREDIENTS

Inactive Ingredients: Dextrose, Magnesium Stearate, Maltodextrin

PURPOSE

Nausea Relief Tablets

Relieves:

• Nausea

• Vomiting

• Indigestion

Uses

For the temporary relief of minor nausea, vomiting, indigestion

Directions

At first sign of symptoms:Adults and children 4 years and older: 1 tablet every 1/2 to 1 hour until symptoms lessen, then continue with standard dosage.

Standard dosage: Adults and children 4 years and older: Take 1-2 tablets every 4 to 6 hours. Do not exceed 12 tablets in 24 hours.

For children under 4, consult your health professional.

Allow tablets to dissolve completely in the mouth, do not swallow

WARNINGS

If pregnant or breast-feeding, ask a health professional before use. Keep out of reach of children. If symptoms persist or worsen, a health professional should be consulted. Do not use if known sensitivity to BHI Nausea or any of its ingredients exists.

KEEP OUT OF REACH OF CHILDREN

ACTIVE INGREDIENT

Each tablet contains: *Anacardium orientale 6X, Argentum nitricum 8X, *Carbo vegetabilis 12X, *Ipecacuanha 6X, *Iodium 12X, *Robinia pseudoacacia 10X, *Sepia 30X 42.9 mg each.

*Natural Ingredients

PACKAGE LABEL

Add image transcription here...